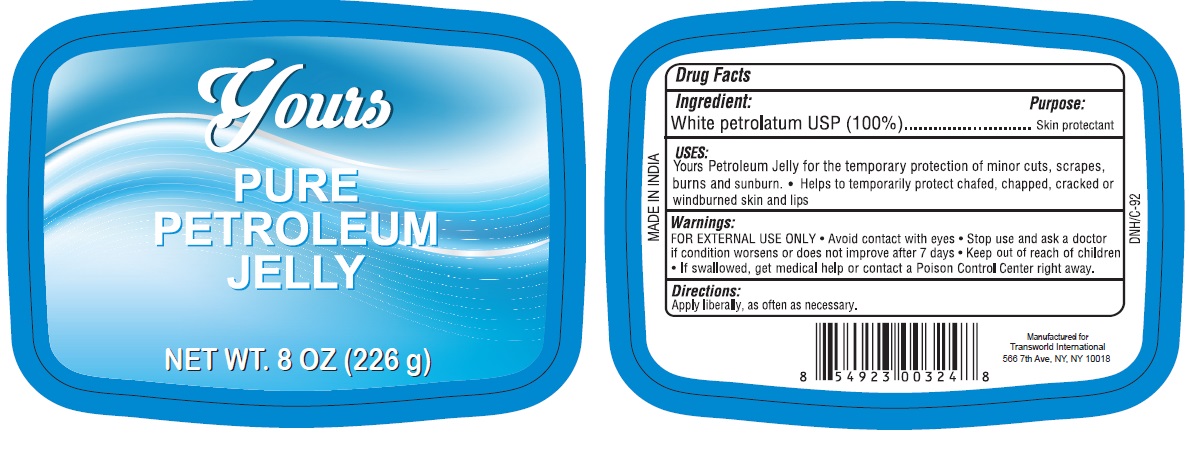 DRUG LABEL: Yours Pure Petroleum
NDC: 71265-001 | Form: JELLY
Manufacturer: TRANSWORLD INTERNATIONAL TRADING CORP.
Category: otc | Type: HUMAN OTC DRUG LABEL
Date: 20170302

ACTIVE INGREDIENTS: PETROLATUM 100 g/100 g

Yours Pure Petroleum Jelly

Active Ingredient

White Petrolatum USP (100%)

Purpose

Skin Protectant

Uses

Yous Petroleum Jelly for the temporary protection of minor cuts, scrapes, burns and sunburn. Helps to temporarily protect chafed, chapped, cracked or windburned skin and lips.

Warnings

For External Use Only.

When using this product

- Avoid contact with eyes.

Stop use and ask a doctor

- If condition worsens or does not improve after 7 days.

Keep out of reach of children

- If swallowed get medical help or contact a Poison Control Center right away.

Directions

Apply liberally, as often as necessary.

Inactive Ingredients

None.

PACKAGE LABEL

PRINCIPAL DISPLAY PANEL

YOURS PURE PETROLEUM JELLY

NET WT. 8OZ. (226 g)